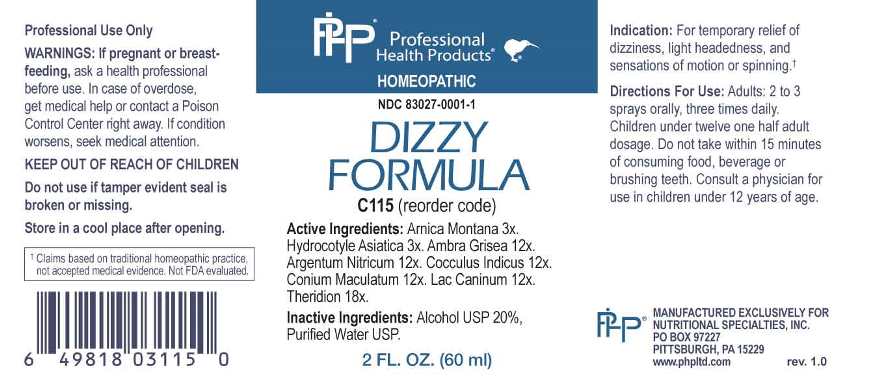 DRUG LABEL: Dizzy Formula
NDC: 83027-0001 | Form: SPRAY
Manufacturer: Nutritional Specialties, Inc.
Category: homeopathic | Type: HUMAN OTC DRUG LABEL
Date: 20230220

ACTIVE INGREDIENTS: ARNICA MONTANA WHOLE 3 [hp_X]/1 mL; CENTELLA ASIATICA FLOWERING TOP 3 [hp_X]/1 mL; AMBERGRIS 12 [hp_X]/1 mL; SILVER NITRATE 12 [hp_X]/1 mL; ANAMIRTA COCCULUS SEED 12 [hp_X]/1 mL; CONIUM MACULATUM FLOWERING TOP 12 [hp_X]/1 mL; CANIS LUPUS FAMILIARIS MILK 12 [hp_X]/1 mL; THERIDION CURASSAVICUM 18 [hp_X]/1 mL
INACTIVE INGREDIENTS: WATER; ALCOHOL

DRUG FACTS:

ACTIVE INGREDIENTS:

Arnica Montana 3X, Hydrocotyle Asiatica 3X, Ambra Grisea 12X, Argentum Nitricum 12X, Cocculus Indicus 12X, Conium Maculatum 12X, Lac Caninum 12X, Theridion 18X.

PURPOSE:

For temporary relief of dizziness, light headedness, and sensations of motion or spinning.†

†Claims based on traditional homeopathic practice, not accepted medical evidence. Not FDA evaluated.

WARNINGS:

Professional Use Only

If pregnant or breast-feeding, ask a health professional before use.

In case of overdose, get medical help or contact a Poison Control Center right away.

If condition worsens, seek medical attention.

KEEP OUT OF REACH OF CHILDREN

Do not use if tamper evident seal is broken or missing.

Store in a cool place after opening

KEEP OUT OF REACH OF CHILDREN:

In case of overdose, get medical help or contact a Poison Control Center right away.

DIRECTIONS:

Adults: 2 to 3 sprays orally, three times daily. Children under twelve one half adult dosage. Do not take within 15 minutes of consuming food, beverage or brushing teeth. Consult a physician for use in children under 12 years of age.

INDICATIONS:

For temporary relief of dizziness, light headedness, and sensations of motion or spinning.†

†Claims based on traditional homeopathic practice, not accepted medical evidence. Not FDA evaluated.

INACTIVE INGREDIENTS:

Alcohol USP 20%, Purified Water USP.

QUESTIONS:

MANUFACTURED EXCLUSIVELY FOR

NUTRITIONAL SPECIALTIES, INC.

PO BOX 97227

PITTSBURG, PA 15229

www.phpltd.com

PACKAGE LABEL DISPLAY:

Professional

Health Products

HOMEOPATHIC

NDC 83027-0001-1

DIZZY

FORMULA

2 FL. OZ (60 ml)